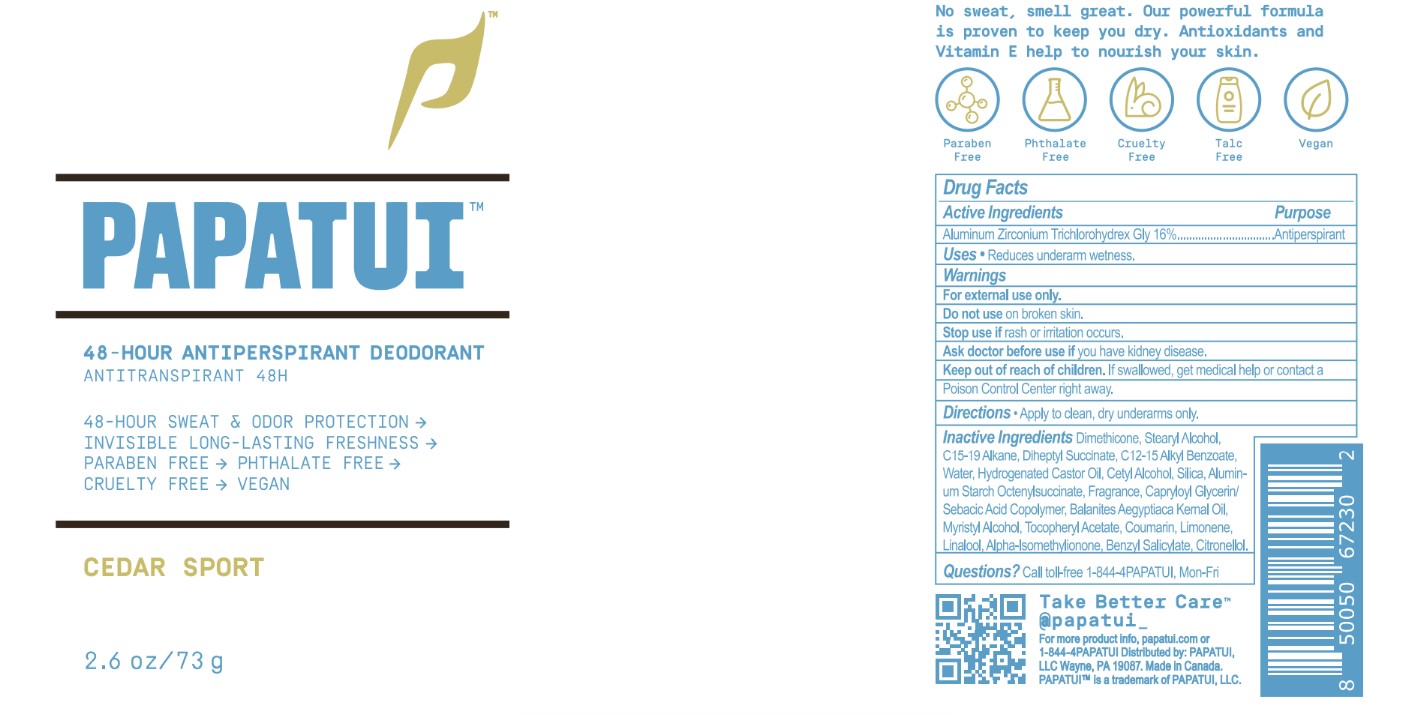 DRUG LABEL: Papatui Antiperspirant Deodorant Cedar Sport
NDC: 83850-101 | Form: STICK
Manufacturer: Forward 7
Category: otc | Type: HUMAN OTC DRUG LABEL
Date: 20241211

ACTIVE INGREDIENTS: ALUMINUM ZIRCONIUM TETRACHLOROHYDREX GLY 160 mg/1 g
INACTIVE INGREDIENTS: ISOMETHYL-.ALPHA.-IONONE; LIMONENE, (+)-; .BETA.-CITRONELLOL, (R)-; DIHEPTYL SUCCINATE; STEARYL ALCOHOL; CAPRYLOYL GLYCERIN/SEBACIC ACID COPOLYMER (2000 MPA.S); CETYL ALCOHOL; ALUMINUM STARCH OCTENYLSUCCINATE; DIMETHICONE; WATER; C15-19 ALKANE; BALANITES AEGYPTIACA SEED OIL; ALKYL (C12-15) BENZOATE; HYDROGENATED CASTOR OIL; SILICON DIOXIDE; COUMARIN; LINALOOL, (+/-)-; BENZYL SALICYLATE; MYRISTYL ALCOHOL; .ALPHA.-TOCOPHEROL ACETATE

Papatui Antiperspirant Deodorant Cedar Sport (NDC 83850-101)

Drug Facts

Active ingredient

Aluminum zirconium trichlorohydrex Gly 16%

Purpose

Antiperspirant

Use

reduces underarm wetness

Warnings

For external use only.

Do not use on broken skin

Stop use if rash or irritation occurs

Ask a doctor before use if you have kidney disease

DOSAGE AND ADMINISTRATION

For external use only.

Keep out of reach of children. If swallowed, get medical help or contact a Poison Control Center right away.

Directions

apply to clean, dry underarms only

Inactive Ingredients

Dimethicone, Stearyl Alcohol, C15-19 Alkane, Diheptyl Succinate, C12-15 Alkyl Benzoate, Water, Hydrogenated Castor Oil, Cetyl Alcohol, Silica, Aluminum Starch Octenylsuccinate, Fragrance, Capryloyl Glycerin/Sebacic Acid Copolymer, Balanites Aegyptiaca Kernal Oil, Myristyl Alcohol, Tocopheryl Acetate, Coumarin, Limonene, Linalool, Alpha-Isomethylionone, Benzyl Salicylate, Citronellol.

Questions?

Questions? Call toll-free 1-844-4PAPATUI, Mon-Fri